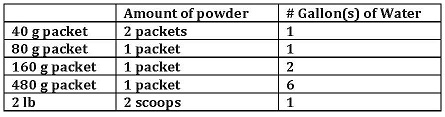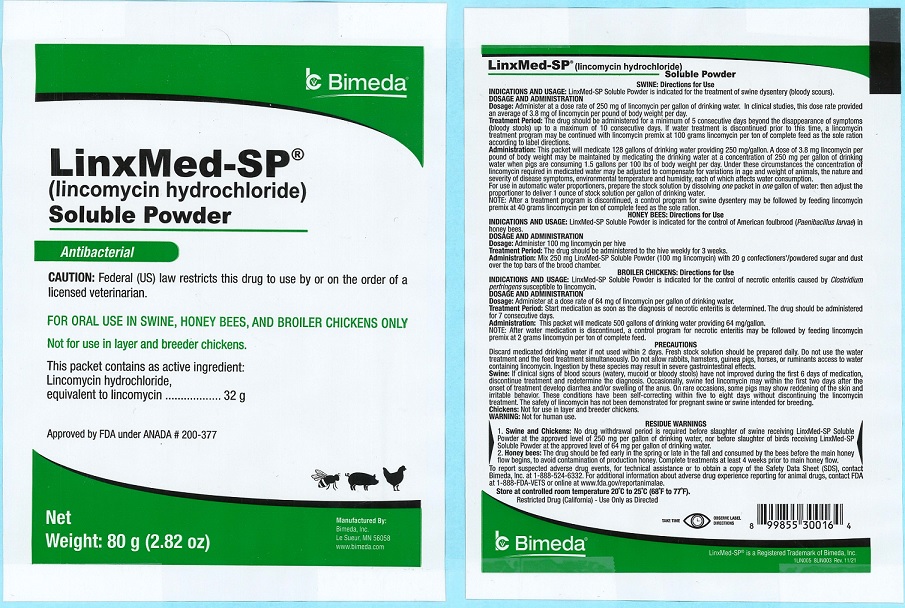 DRUG LABEL: LinxMed-SP
NDC: 61133-5482 | Form: POWDER
Manufacturer: Bimeda, Inc.
Category: animal | Type: PRESCRIPTION ANIMAL DRUG LABEL
Date: 20240327

ACTIVE INGREDIENTS: Lincomycin Hydrochloride  32 g/80 g

DESCRIPTION

LinxMed-SP®
(lincomycin hydrochloride) Soluble Powder
Antibacterial
CAUTION: Federal (US) law restricts this drug to use by or on the order of a licensed veterinarian.
FOR ORAL USE IN SWINE, HONEY BEES, AND BROILER CHICKENS ONLY.
Not for use in layer and breeder chickens.

The 40 g packet contains as active ingredient:
Lincomycin hydrochloride equivalent to lincomycin.................16 g

The 80 g packet contains as active ingredient:
Lincomycin hydrochloride equivalent to lincomycin.................32 g

The 160 g packet contains as active ingredient:
Lincomycin hydrochloride equivalent to lincomycin.................64 g

The 480 g packet contains as active ingredient:
Lincomycin hydrochloride equivalent to lincomycin.................192 g

Each gram of powder in the 2 lb container contains as active ingredient:
Lincomycin hydrochloride equivalent to lincomycin.................400 mg

Approved by FDA under ANADA # 200-377

INDICATIONS AND USAGE

SWINE: Directions for Use
INDICATIONS AND USAGE: LinxMed-SP Soluble Powder is indicated for the treatment of swine dysentery (bloody scours).

DOSAGE AND ADMINISTRATION
Dosage: Administer at a dose rate of 250 mg of lincomycin per gallon of drinking water. In clinical studies, this dose rate provided an average of 3.8 mg of lincomycin per pound of body weight per day.

Treatment Period: The drug should be administered for a minimum of 5 consecutive days beyond disappearance of symptoms (bloody stools) up to a maximum of 10 consecutive days. If water treatment is discontinued prior to this time, a lincomycin treatment program may be continued with lincomycin premix at 100 grams lincomycin per ton of complete feed as the sole ration according to label directions.

Administration:
The 40 g packet will medicate 64 gallons of drinking water providing 250 mg/gallon.
The 80 g packet will medicate 128 gallons of drinking water providing 250 mg/gallon.
The 160 g packet will medicate 256 gallons of drinking water providing 250 mg/gallon.
The 480 g packet will medicate 768 gallons of drinking water providing 250 mg/gallon.
One scoop (provided) of powder from the 2 lb container will medicate 64 gallons of drinking water providing 250 mg/gallon.

A dose of 3.8 mg lincomycin per pound of body weight may be maintained by medicating the drinking water at a concentration of 250 mg per gallon of drinking water when pigs are consuming 1.5 gallons per 100 lbs of body weight per day. Under these circumstances the concentration of lincomycin required in medicated water may be adjusted to compensate for variations in age and weight of animals, the nature and severity of disease symptoms, environmental temperature and humidity, each of which affects water consumption.

For use in automatic water proportioners, prepare the stock solution by dissolving the amount of powder indicated (in packets or scoops) below into the number of gallons of water indicated; then adjust the proportioner to deliver 1 ounce of stock solution per gallon of drinking water.

NOTE: After a treatment program is discontinued, a control program for swine dysentery may be followed by feeding lincomycin premix at 40 grams lincomycin per ton of complete feed as the sole ration.

HONEY BEES: Directions for Use
INDICATIONS AND USAGE: LinxMed-SP Soluble Powder is indicated for the control of American foulbrood (Paenibacillus larvae) in honey bees.

DOSAGE AND ADMINISTRATION
Dosage: Administer 100 mg lincomycin per hive

Treatment Period: The drug should be administered to the hive weekly for 3 weeks.

Administration: Mix 250 mg LinxMed-SP Soluble Powder (100 mg lincomycin) with 20 g confectioners’/powdered sugar and dust over the tops of the brood chamber.

BROILER CHICKENS: Directions for Use
INDICATIONS AND USAGE: LinxMed-SP Soluble Powder is indicated for the control of necrotic enteritis caused by Clostridium perfringens susceptible to lincomycin.

DOSAGE AND ADMINISTRATION
Dosage: Administer at a dose rate of 64 mg of lincomycin per gallon of drinking water.

Treatment Period: Start medication as soon as the diagnosis of necrotic enteritis is determined. The drug should be administered for 7 consecutive days.

Administration:
The 40 g packet will medicate 250 gallons of drinking water providing 64 mg/gallon.
The 80 g packet will medicate 500 gallons of drinking water providing 64 mg/gallon.
The 160 g packet will medicate 1,000 gallons of drinking water providing 64 mg/gallon.
The 480 g packet will medicate 3,000 gallons of drinking water providing 64 mg/gallon.
One scoop (provided) of powder from the 2 lb container will medicate 250 gallons of drinking water providing 64 mg/gallon.

NOTE: After water medication is discontinued, a recommended control program for necrotic enteritis consists of feeding lincomycin premix at 2 grams lincomycin per ton of complete feed.

PRECAUTIONS
Discard medicated drinking water if not used within 2 days. Fresh stock solution should be prepared daily. Do not use the water treatment and the feed treatments simultaneously. Do not allow rabbits, hamsters, guinea pigs, horses or ruminants access to water containing lincomycin treatment. Ingestion by these species may result in severe gastrointestinal effects.

Swine: If clinical signs of bloody scours (watery, mucoid or bloody stools) have not improved during the first 6 days of medication, discontinue treatment and redetermine the diagnosis. Occasionally, swine fed lincomycin may within the first two days after the onset of treatment develop diarrhea and/or swelling of the anus. On rare occasions, some pigs may show reddening of the skin and irritable behavior. These conditions have been self-correcting within five to eight days without discontinuing the lincomycin treatment. 4. The safety of lincomycin has not been demonstrated for pregnant swine or swine intended

Chickens: Not for use in layer and breeder chickens.

WARNING: Not for human use.

RESIDUE WARNINGS:
1. Swine and Chickens: No drug withdrawal period is required before slaughter of swine receiving LinxMed-SP Soluble Powder at the approved level of 250 mg per gallon of drinking water, nor before slaughter of birds receiving LinxMed-SP Soluble Powder at the approved level of 64 mg per gallon of drinking water.

2. Honey bees: The drug should be fed early in the sprint or late in the fall and consumed by the bees before the main honey flow begins, to avoid contamination of production honey. Complete treatments at least 4 weeks prior to main honey flow.

To report suspected adverse drug events, for technical assistance or to obtain a copy of the Safety Data Sheet (SDS), contact Bimeda, Inc. at 1-888-524-6332. For additional information about adverse drug experience reporting for animal drugs, contact FDA at 1-888-FDA-VETS or online at www.fda.gov/reportanimalae.

STORAGE AND HANDLING

Store at controlled room temperature 20°C to 25°C (68°F to 77°F).

Restricted Drug (California) – Use Only as Directed